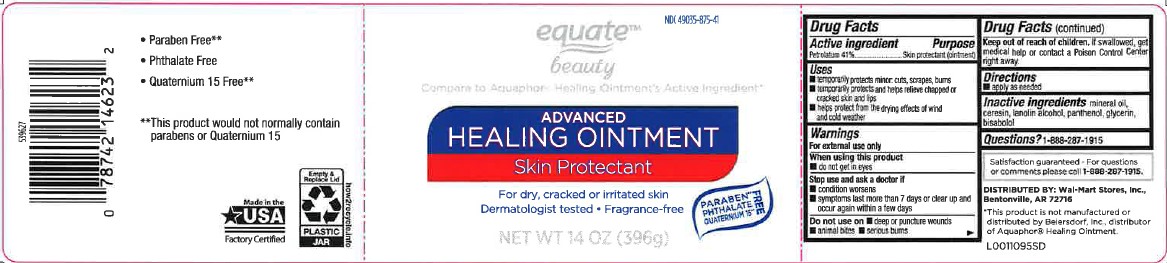 DRUG LABEL: Advanced Healing
NDC: 49035-875 | Form: OINTMENT
Manufacturer: Walmart Inc.
Category: otc | Type: HUMAN OTC DRUG LABEL
Date: 20260227

ACTIVE INGREDIENTS: PETROLATUM 410 mg/1 g
INACTIVE INGREDIENTS: MINERAL OIL; CERESIN; LANOLIN ALCOHOLS; PANTHENOL; GLYCERIN; LEVOMENOL

Equate 247.001/247AC
Healing Ointment for Dry and Cracked Skin

Active ingredient

Petrolaturm 41%

Purpose

Skin protectant (ointment)

Uses

- temporarily protects minor: cuts, scrapes, burns
- temporarily protects and helps relieve chapped and cracked skin and lips
- helps protect from the drying effects of wind and cold weather

Warnings

For external use only

When using this product

- do not get in eyes

Stop use and ask a doctor if

- condition worsens
- symptoms last more than 7 days or clear up and occur again within a few days

Do not use on

- deep or puncture wounds
- animal bites
- serious burns

Keep out of reach of children.

If swallowed get medical help or contract a Poison Control Center right away.

Directions

- apply as needed

Inactive ingredients

minerol oil, ceresin, lanolin alcohol, panthenol, glycerin, bisabolol

Questions?

1-888-287-1915

ADVERSE REACTION

- Paraben free **
- Phthalate free
- Quaternium 15 free**

**This product would not normally contain parabens or quaternium 15

Made in the USA with 90% or more US parts factory certified

Empty & Replace Lid

PLASTIC JAR

how2recycle.info

Satisfaction guaranteed - For Questions or comments please call 1-888-287-1915.

Distributed by: Wal-Mart Stores, Inc.,

Bentonville, AR 72716

Disclaimer

*This product is not manufactured or distributed by Beiersdorf Inc., distributor Aquaphor®Healing Ointment.

principal display panel

NDC 49035-875-41

equate™

beauty

Compare to Aquaphor Healing Ointment's Active Ingredient*

Advanced

Healing Ointment

Skin Protectant

For Dry, Cracked, or Irritated Skin

Dermatologist tested • Fragrance-free

Paraben**, phthalate, Quaternium 15** FREE

NET WT 14 OZ (396 g)